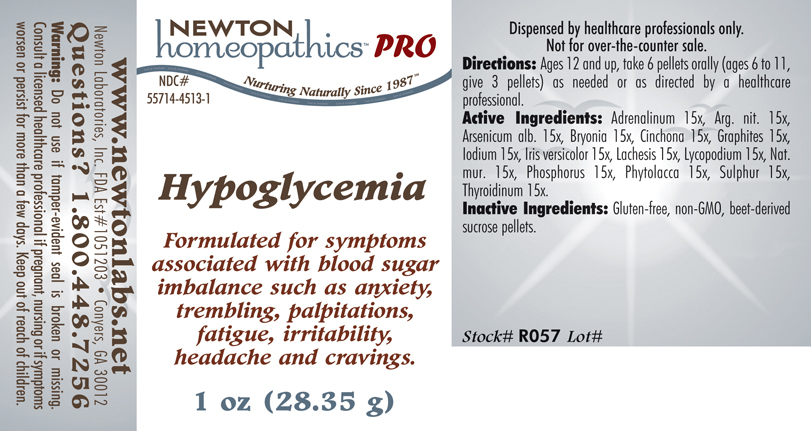 DRUG LABEL: Hypoglycemia 
NDC: 55714-4513 | Form: PELLET
Manufacturer: Newton Laboratories, Inc.
Category: homeopathic | Type: HUMAN PRESCRIPTION DRUG LABEL
Date: 20110601

ACTIVE INGREDIENTS: Epinephrine 15 [hp_X]/1 g; Silver Nitrate 15 [hp_X]/1 g; Arsenic Trioxide 15 [hp_X]/1 g; Bryonia Alba Root 15 [hp_X]/1 g; Cinchona Officinalis Bark 15 [hp_X]/1 g; Graphite 15 [hp_X]/1 g; Iodine 15 [hp_X]/1 g; Iris Versicolor Root 15 [hp_X]/1 g; Lachesis Muta Venom 15 [hp_X]/1 g; Lycopodium Clavatum Spore 15 [hp_X]/1 g; Sodium Chloride 15 [hp_X]/1 g; Phosphorus 15 [hp_X]/1 g; Phytolacca Americana Root 15 [hp_X]/1 g; Sulfur 15 [hp_X]/1 g; Thyroid, Unspecified 15 [hp_X]/1 g
INACTIVE INGREDIENTS: Sucrose

Hypoglycemia

INDICATIONS & USAGE SECTION

Hypoglycemia Formulated for symptoms associated with blood sugar imbalance such as anxiety, trembling, palpitations, fatigue, irritability, headache and cravings.

DOSAGE & ADMINISTRATION SECTION

Directions: Ages 12 and up, take 6 pellets orally (ages 6 to 11, give 3 pellets) one to four times daily or as directed by a healthcare professional.

ACTIVE INGREDIENT SECTION

Adrenalinum 15x, Arg. nit. 15x, Arsenicum alb. 15x, Bryonia 15x, Cinchona 15x, Graphites 15x, Iodium 15x, Iris versicolor 15x, Lachesis 15x, Lycopodium 15x, Nat.mur. 15x, Phosphorus 15x, Phytolacca 15x, Sulphur 15x, Thyroidinum 15x.

PURPOSE SECTION

Formulated for symptoms associated with blood sugar imbalance such as anxiety, trembling, palpitations, fatigue, irritability, headache and cravings.

INACTIVE INGREDIENT SECTION

Inactive Ingredients: Gluten-free, non-GMO, beet-derived sucrose pellets.

QUESTIONS? SECTION

www.newtonlabs.net Newton Laboratories, Inc. FDA Est # 1051203 - Conyers, GA 30012
Questions? 1.800.448.7256

WARNINGS SECTION

Warning: Do not use if tamper - evident seal is broken or missing. Consult a licensed healthcare professional if pregnant, nursing or if symptoms worsen or persist for more than a few days. Keep out of reach of children.

PREGNANCY OR BREAST FEEDING SECTION

Consult a licensed healthcare professional if pregnant, nursing or if symptoms worsen or persist for more than a few days.

KEEP OUT OF REACH OF CHILDREN SECTION

Keep out of reach of children.